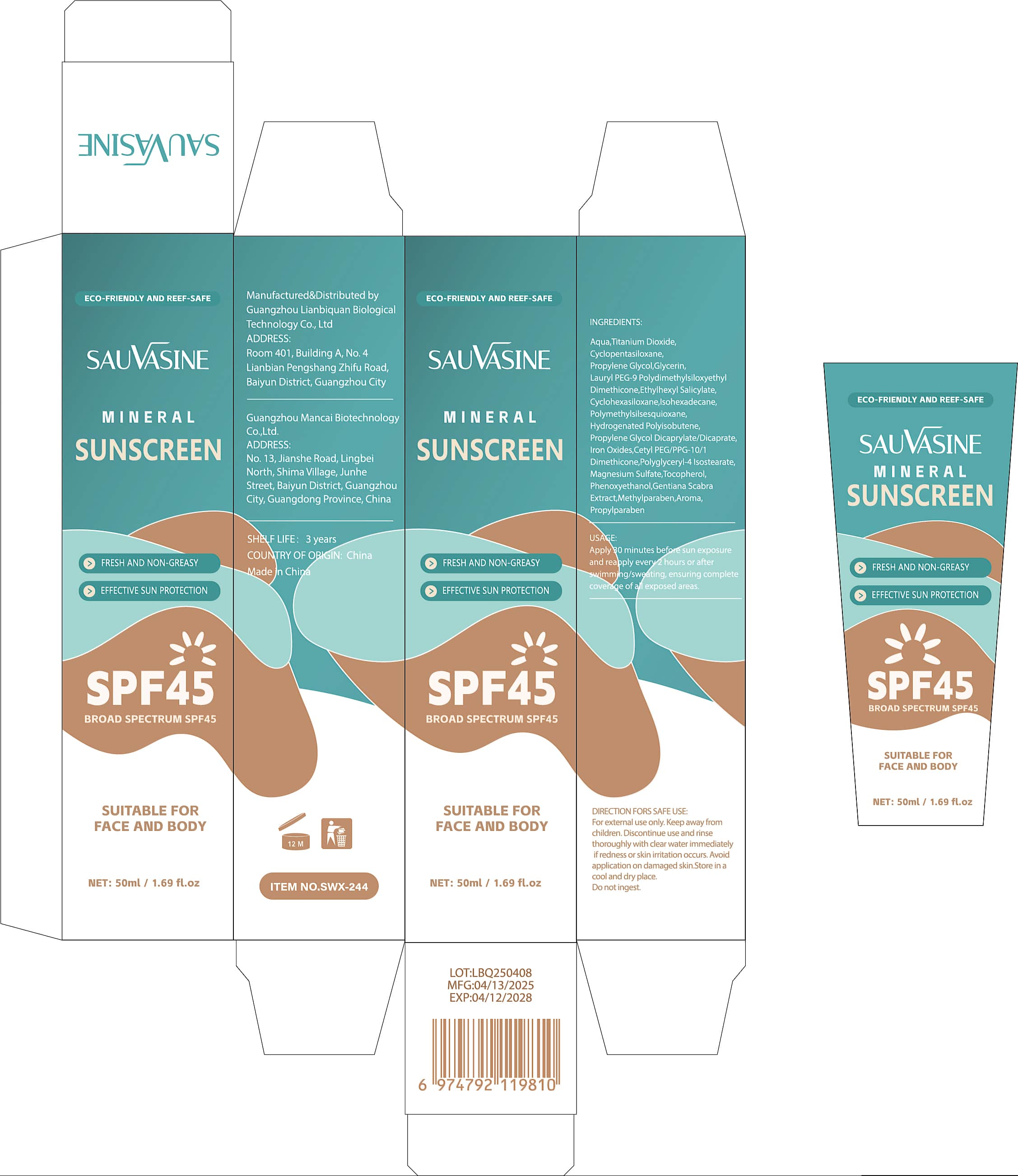 DRUG LABEL: Mineral Sunscreen
NDC: 84778-094 | Form: CREAM
Manufacturer: Guangzhou Yixin Cross-border E-commerce Co., Ltd.
Category: otc | Type: HUMAN OTC DRUG LABEL
Date: 20250923

ACTIVE INGREDIENTS: TITANIUM DIOXIDE 8 g/100 g
INACTIVE INGREDIENTS: AQUA; NIACINAMIDE

Active ingredients (in each film)

Titanium Dioxide 8%

Purpose

sunscreen

Uses

Helps prevent sunburn

Warnings

For external use only.
When using this product:
- Do not get into eyes. Rinse with water to remove.
Stop use and ask a doctor if:
- Rash occurs.
Keep out of reach of children.
If swallowed, get medical help or contact a Poison Control Center right away.

Do not use if you:

Do not use
- On damaged or broken skin.
- If you have known allergies to any ingredient in the product.

Dosage and administration

Stop use and ask a doctor if- Redness develops.

When using this product you may experience:

Do not get into eyes. Rinse with water to remove

Stop use and ask a doctor if:

- Irritation or rash persists.
- Redness develops.

Contraindications

Keep out of reach of children.
If swallowed, get medical help or contact a Poison Control Center right away.

Inactive ingredients

Aqua,Cyclopentasiloxane,Propylene Glycol,Glycerin,Lauryl PEG-9 PolydimethylsiloxyethylDimethicone,Ethylhexyl Salicylate,Cyclohexasiloxane,lsohexadecane,Polymethylsilsesquioxane,Hydrogenated Polyisobutene,Propylene Glycol Dicaprylate/Dicaprate,lron Oxides,Cetyl PEG/PPG-10/1Dimethicone,Polyglyceryl-4 lsostearate,Magnesium Sulfate,Tocopherol,Phenoxyethanol,Gentiana ScabraExtract,Methylparaben,Aroma,Propylparaben